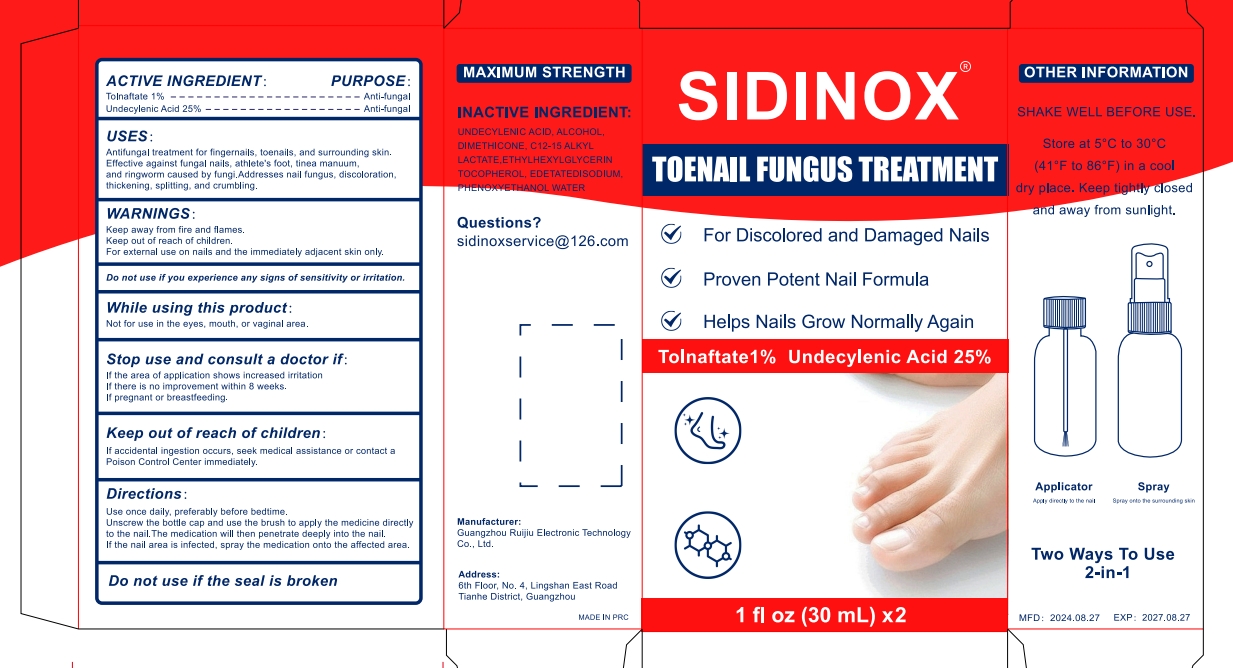 DRUG LABEL: SIDINOX TOENAIL FUNGUS TREATMENT  Liquid
NDC: 83767-801 | Form: LIQUID
Manufacturer: Guangzhou Ruijiu Electronic Technology Co., Ltd.
Category: otc | Type: HUMAN OTC DRUG LABEL
Date: 20240905

ACTIVE INGREDIENTS: UNDECYLENIC ACID 25 g/100 mL; TOLNAFTATE 1 g/100 mL
INACTIVE INGREDIENTS: ALCOHOL; WATER; DIMETHICONE; C12-15 ALKYL LACTATE; ETHYLHEXYLGLYCERIN; TOCOPHEROL; EDETATE DISODIUM; PHENOXYETHANOL

SIDINOX TOENAIL FUNGUS TREATMENT Liquid

SIDINOX TOENAIL FUNGUS TREATMENT Liquid

ACTIVE INGREDIENT

TOLNAFTATE 1%
UNDECYLENIC ACID 25%

PURPOSE

Anti-fungal

INDICATIONS AND USAGE

Antifungal treatment for fingernails, toenails, and surrounding skin.Efective against fungal nails, athlete's fcot, tinea manuum,and ringworm caused by fungi.Addresses nail fungus, discoloralionthickening, splitling, and crumbling.

WARNINGS

Keep away from fire and flames.
Keep out of reach of children.
For external use on nails and the immediately adjacent skin only.

Do not use ifyou experience any signs of sensitivity or irritation

WHEN USING

While using this product:Not for use in the eyes, mouth, or vaginal area.

Stop use and consult a doctor if:
If the area of application shows increased irritation
If there is no improvement within 8 weeks.
If pregnant or breaslleeding.

Keep out of reach of children:
If accidental ingestion occurs, seek medical assistance or contact aPoison Control Center immediately.

DOSAGE AND ADMINISTRATION

Use once daily, preferably before bedtime.
Unscrew the bottle cap and use the brush to apply the medicine directlyto the nail.The medication will then penetrate deeply into the nail.
If the nail area is infected, spray the medication onto the affected area.

STORAGE AND HANDLING

SHAKE WELL BEFORE USE.
Store at 5'C to 30°0(41'F to 86°F) in a cool
dry place. Keep tighosedand away from sunlight.

INACTIVE INGREDIENT

ALCOHOL
DIMETHICONE
C12-15 ALKYL LACTATE
ETHYLHEXYLGLYCERIN
TOCOPHEROL
EDETATE DISODIUM
PHENOXYETHANOL
WATER